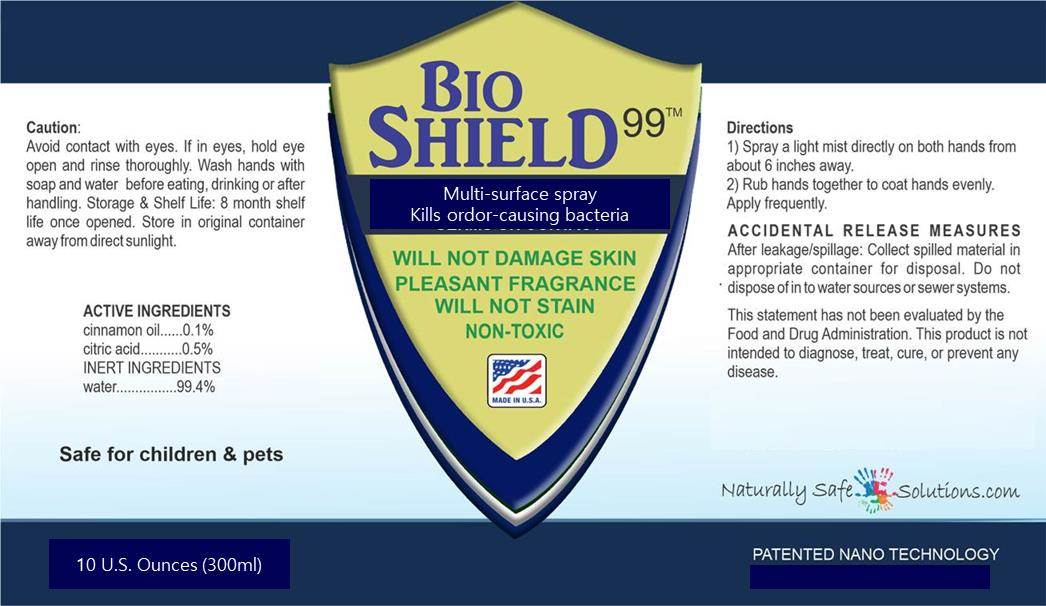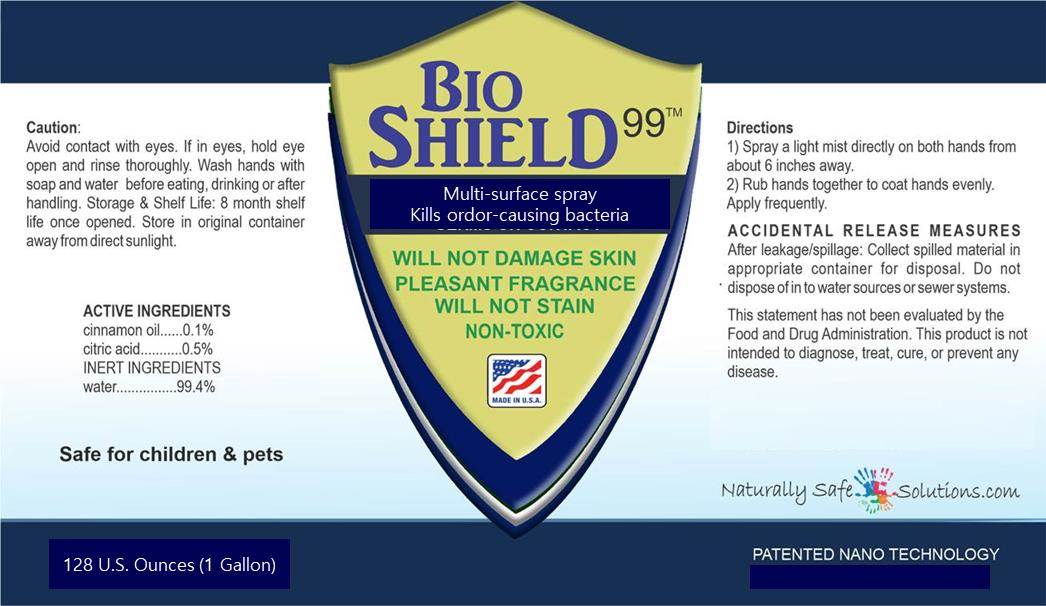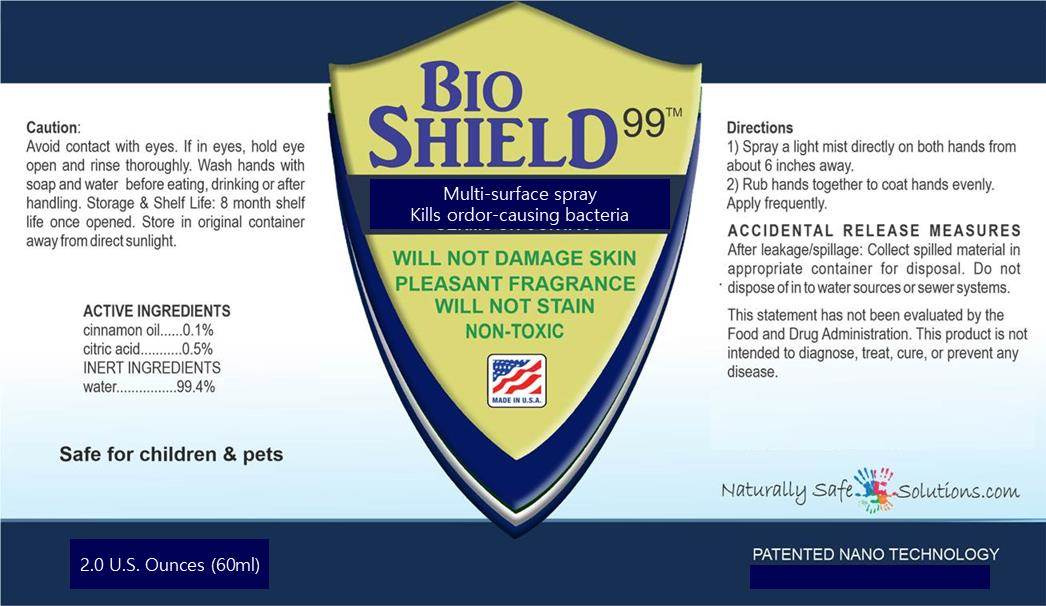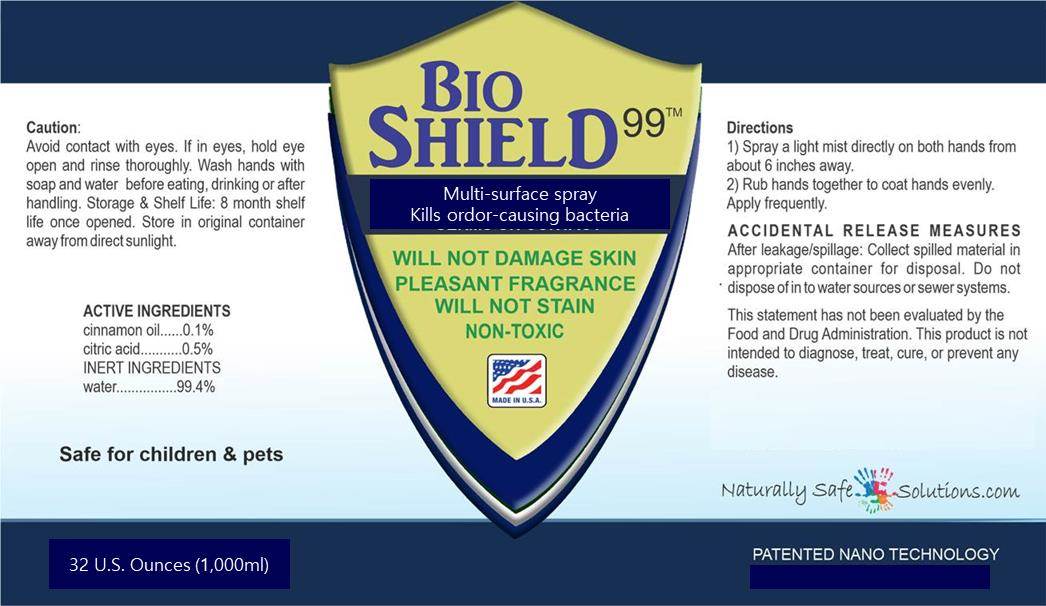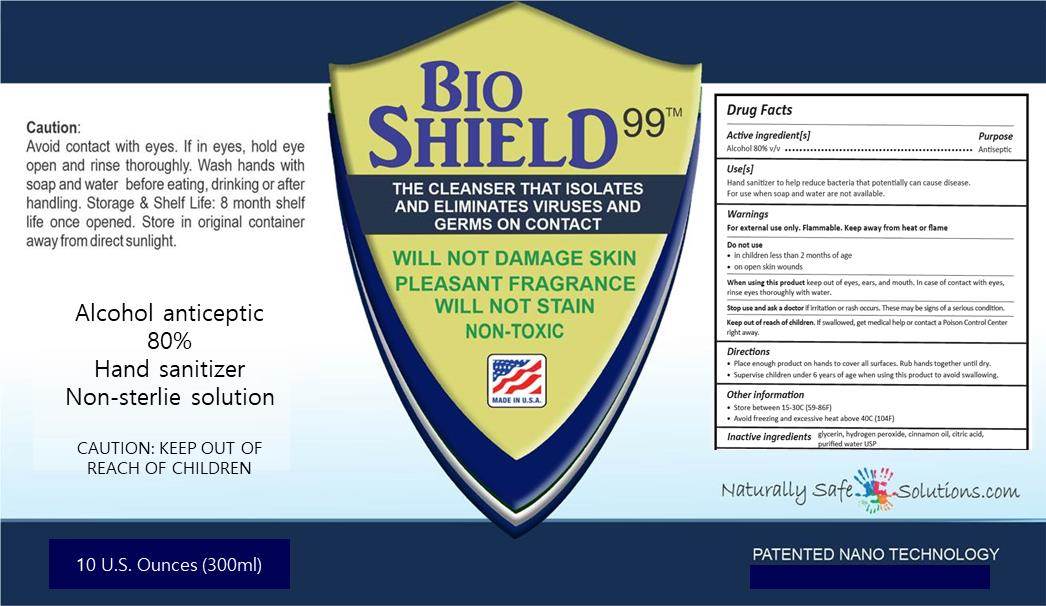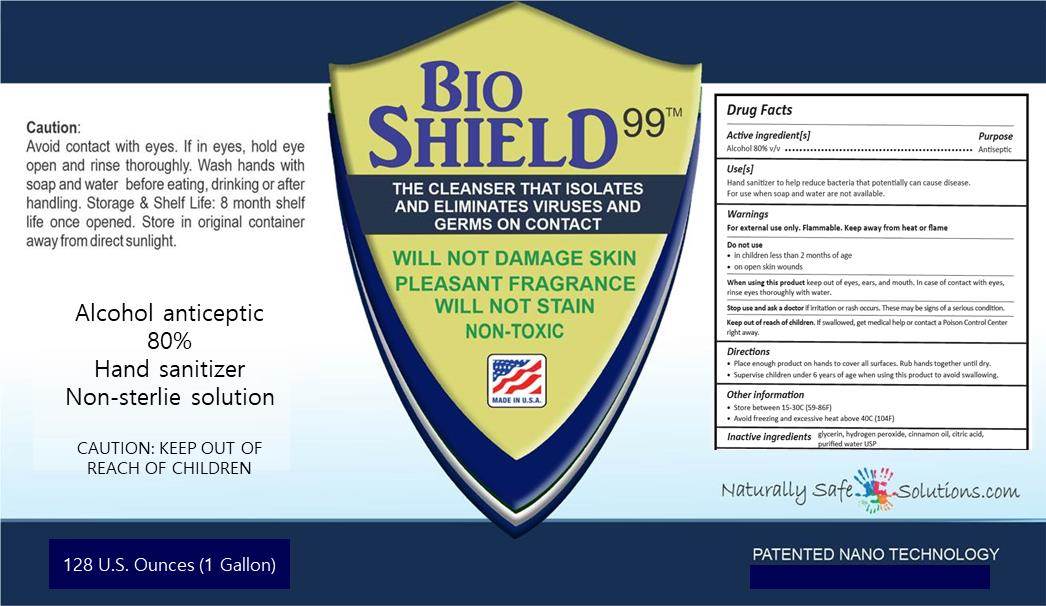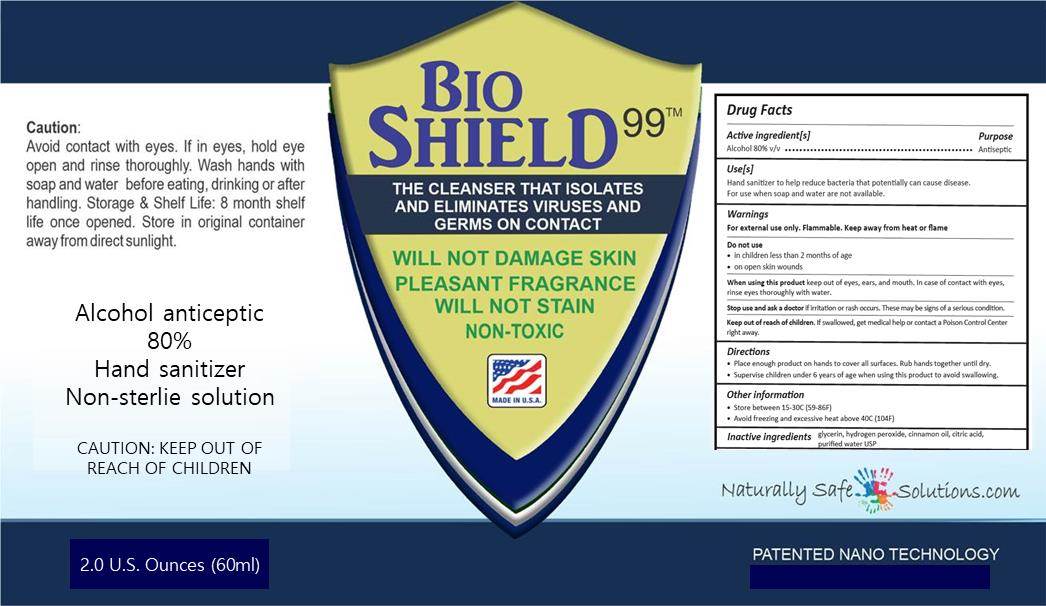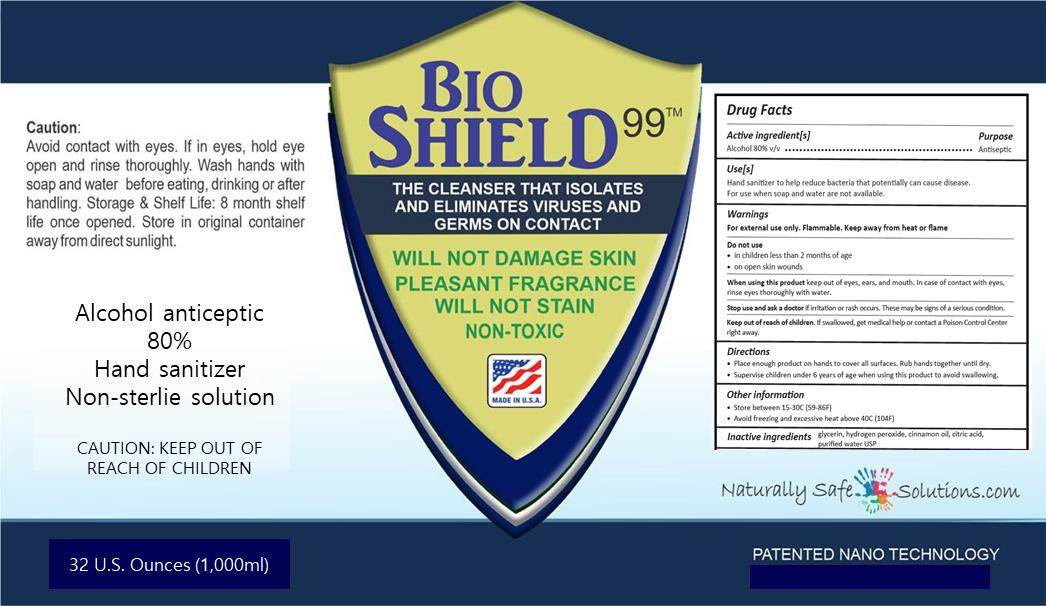 DRUG LABEL: BioShield 99 Alcohol
NDC: 81627-025 | Form: SPRAY
Manufacturer: Naturally Safe Solutions, LLC
Category: otc | Type: HUMAN OTC DRUG LABEL
Date: 20210304

ACTIVE INGREDIENTS: ALCOHOL 800 mL/1000 mL
INACTIVE INGREDIENTS: CINNAMON OIL; WATER; ANHYDROUS CITRIC ACID; GLYCERIN; HYDROGEN PEROXIDE

Product 81627-015 Active Ingredients: ALCOHOL
Product 81627-025 Active Ingredients: CITRIC ACID MONOHYDRATE, CINNAMON OIL

DOSAGE AND ADMINISTRATION

Product NDC: 81311-025:

Directions: Place enough product on hands to cover all surfaces. Rub hands together until dry.
Supervise children under 6 years of age when using this product to avoid swallowing.

INACTIVE INGREDIENT

Product NDC: 81311-025:

HYDROGEN PEROXIDE, GLYCERIN, CINNAMON OIL, ANHYDROUS CITRIC ACID, WATER

INDICATIONS AND USAGE

Product NDC: 81311-025:

Use(s): Hand Sanitizer to help reduce bacteria that potentially can cause disease. For use when soap and water are not available.

KEEP OUT OF REACH OF CHILDREN

Product NDC: 81311-025:

If swallowed, get medical help or contact a Poison Control Center right away at 1-800-222-1222.

PURPOSE

Product NDC: 81311-025:

Antiseptic

ACTIVE INGREDIENT

Product NDC: 81311-025:

Alcohol 80% v/v

WARNINGS

Product NDC: 81311-025:

For external use only. Flammable. Keep away from heat or flame

DO NOT USE

Product NDC: 81311-025:

in children less than 2 months of age • on open skin wounds

WHEN USING

Product NDC: 81311-025:

keep out of eyes, ears, and mouth. In case of contact with eyes, rinse eyes thoroughly with water.

STOP USE

Product NDC: 81311-025:

if irritation or rash occurs. These may be signs of a serious condition.

OTHER SAFETY INFORMATION

Product NDC: 81311-025:

Store between 15-30C (59-86F)

• Avoid freezing and excessive heat above 40C (104F)

PACKAGE LABEL

60 mL NDC: 81627-015-02

300 mL NDC: 81627-015-10

1000 mL NDC: 81627-015-32

3785 mL NDC: 81627-015-50

60 mL NDC: 81627-025-02

300 mL NDC: 81627-025-10

1000 mL NDC: 81627-025-32

3785 mL NDC: 81627-025-50